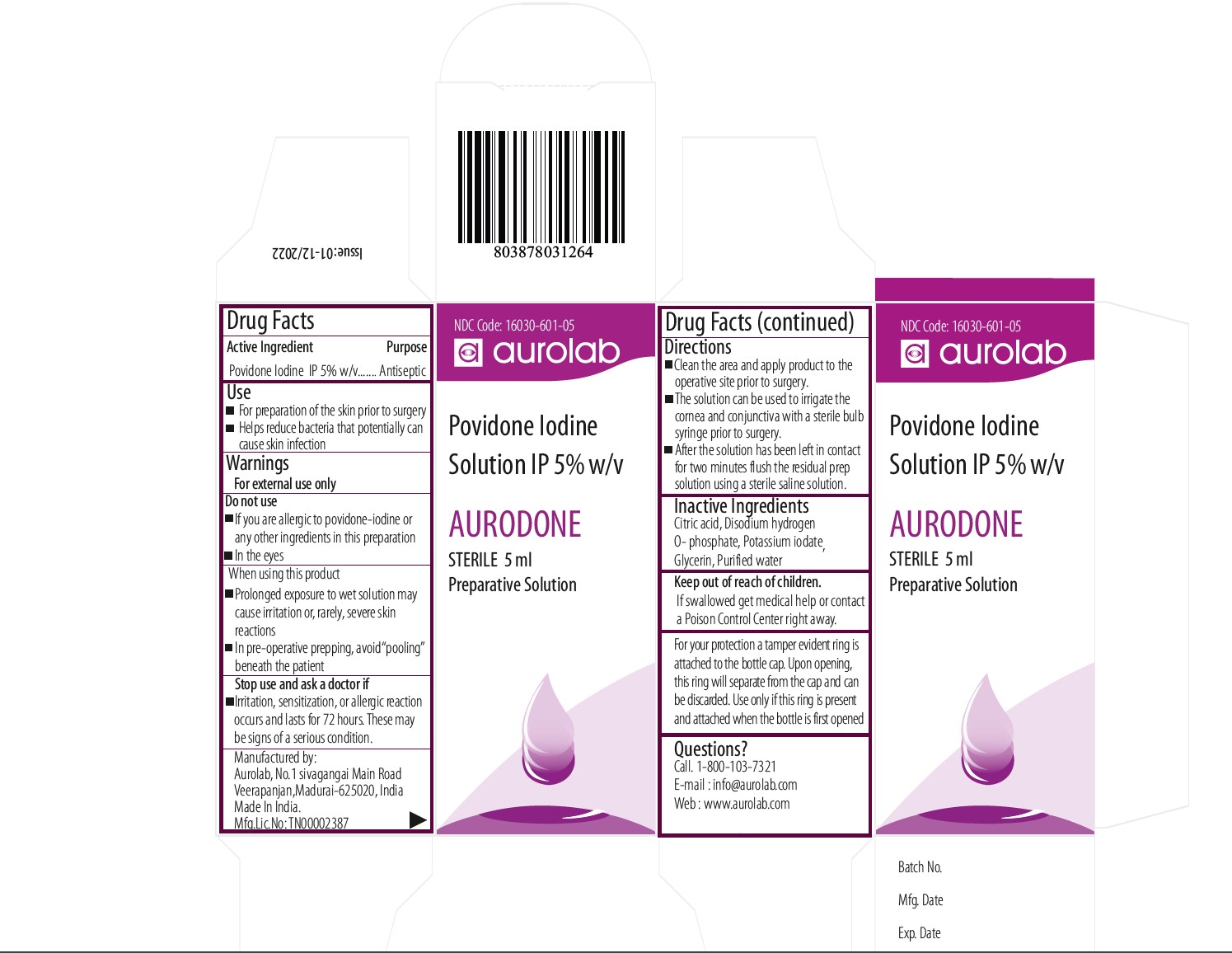 DRUG LABEL: Aurodone Povidone Iodine 5 % Opthalmic Solution
NDC: 16030-601 | Form: SOLUTION
Manufacturer: Aurolab
Category: otc | Type: HUMAN OTC DRUG LABEL
Date: 20250106

ACTIVE INGREDIENTS: POVIDONE-IODINE 5 mg/1 mL
INACTIVE INGREDIENTS: GLYCERIN; WATER; CITRIC ACID ACETATE; POTASSIUM IODATE; DISODIUM HYDROGEN CITRATE

ACTIVE INGREDIENT

Povidone Iodine IP 5% w/v.

INACTIVE INGREDIENT

1. Citric acid
2. Disodium hydrogen O- phosphate, Potassium iodate
3. Glycerin
4. Purified water

USE

- For preparation of the skin prior to surgery
- Helps reduce bacteria that potentially can

cause skin infection

QUESTIONS

Call. 1-800-103-7321,

E-mail : info@aurolab.com
Web : www.aurolab.com

KEEP OUT OF REACH OF CHILDREN

If swallowed get medical help or contact a Poison Control Center right away.

STOP USE

Irritation, sensitization, or allergic reaction
occurs and lasts for 72 hours. These may
be signs of a serious condition.

DO NOT USE

1. If you are allergic to povidone-iodine or
  any other ingredients in this preparation
  In the eyes

WARNINGS

For External use only

INDIACATIONS AND USAGE

Prolonged exposure to wet solution may
cause irritation or, rarely, severe skin
reactions
In pre-operative prepping, avoid “pooling”
beneath the patient

Purpose

Antiseptic

Dose

- Clean the area and apply product to the operative site prior to surgery.
- The solution can be used to irrigate the cornea and conjunctiva with a sterile bulb syringe prior to surgery.
- After the solution has been left in contact for two minutes flush the residual prep solution using a sterile saline solution.